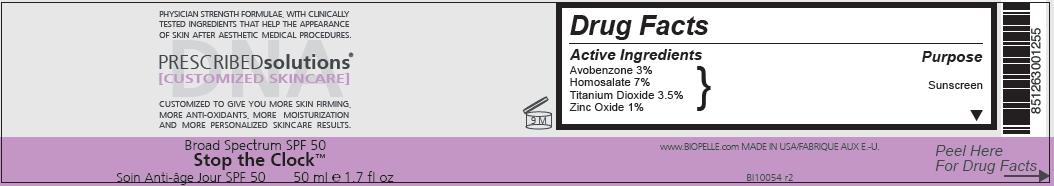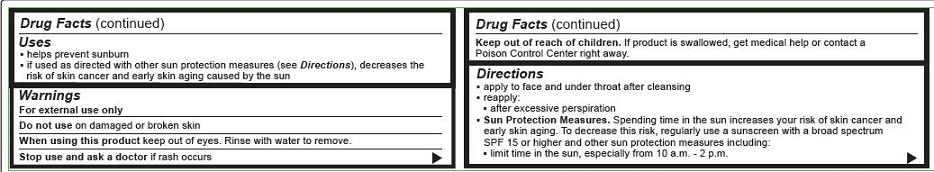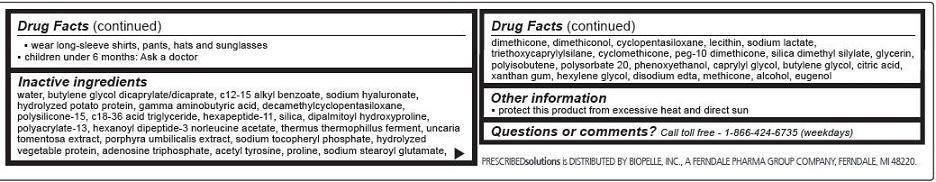 DRUG LABEL: STOP THE CLOCK BROAD SPECTRUM SPF 50
NDC: 42485-006 | Form: CREAM
Manufacturer: Biopelle, Inc.
Category: otc | Type: HUMAN OTC DRUG LABEL
Date: 20110912

ACTIVE INGREDIENTS: AVOBENZONE 30 mg/1 mL; HOMOSALATE 70 mg/1 mL; TITANIUM DIOXIDE 35 mg/1 mL; ZINC OXIDE 10 mg/1 mL
INACTIVE INGREDIENTS: WATER; BUTYLENE GLYCOL; ALKYL (C12-15) BENZOATE; HYALURONATE SODIUM; POTATO; .GAMMA.-AMINOBUTYRIC ACID; CYCLOMETHICONE 5; POLYSILICONE-15; C18-36 ACID TRIGLYCERIDE ; SILICON DIOXIDE; DIPALMITOYL HYDROXYPROLINE; HEXANOYL DIPEPTIDE-3 NORLEUCINE ACETATE; CAT'S CLAW; PORPHYRA UMBILICALIS; ADENOSINE TRIPHOSPHATE; N-ACETYL-TYROSINE; PROLINE; SODIUM STEAROYL GLUTAMATE; DIMETHICONE; CYCLOMETHICONE 5; SODIUM LACTATE; TRIETHOXYCAPRYLYLSILANE; CYCLOMETHICONE; GLYCERIN; POLYSORBATE 20; PHENOXYETHANOL; CAPRYLYL GLYCOL; BUTYLENE GLYCOL; CITRIC ACID MONOHYDRATE; XANTHAN GUM; HEXYLENE GLYCOL; EDETATE DISODIUM; ALCOHOL; EUGENOL; POLYISOBUTYLENE (1000 MW); DIMETHICONOL (41 MPA.S); LECITHIN, SOYBEAN

Stop the Clock Broad Spectrum SPF 50

Active Ingredients

Avobenzone 3%

Homosalate 7%

Titanium Dioxide 3.5%

Zinc Oxide 1%

Purpose

Sunscreen

Uses

- helps prevent sunburn
- if used as directed with other sun protection measures (see Directions), decreases the risk of skin cancer and early skin aging caused by the sun

Warnings

For external use only

Do not use on damaged or broken skin

When using this product keep out of eyes. Rinse with water to remove.

Stop use and ask a doctor if rash occurs

Keep out of reach of children. If product is swallowed, get medical help or contact a Poison Control Center right away.

Directions

- apply to face and under throat after cleansing
- reapply:
-
  - after excessive perspiration
- Sun Protection Measures. Spending time in the sun increases your risk of skin cancer and early skin aging. To decrease this risk, regularly use a sunscreen with a broad spectrum SPF 15 or higher and other sun protection measures including:
-
  - limit time in the sun, especially from 10 a.m. - 2 p.m.
-
  - wear long-sleeve shirts, pants, hats and sunglasses
- children under 6 months: Ask a doctor

Inactive ingredients

water, butylene glycol dicaprylate/dicaprate, c12-15 alkyl benzoate, sodium hyaluronate, hydrolyzed potato protein, gamma aminobutyric acid, decamethylcyclopentasiloxane, polysilicone-15, c18-36 acid triglyceride, hexapeptide-11, silica, dipalmitoyl hydroxyproline, polyacrylate-13, hexanoyl dipeptide-3 norleucine acetate, thermus thermophillus ferment, uncaria tomentosa extract, porphyra umbilicalis extract, sodium tocopheryl phosphate, hydrolyzed vegetable protein, adenosine triphosphate, acetyl tyrosine, proline, sodium stearoyl glutamate, dimethicone, dimethiconol, cyclopentasiloxane, lecithin, sodium lactate, triethoxycaprylylsilane, cyclomethicone, peg-10 dimethicone, silica dimethyl silylate, glycerin, polyisobutene, polysorbate 20, phenoxyethanol, caprylyl glycol, butylene glycol, citric acid, xantham gum, hexylene glycol, disodium edta, methicone, alcohol, eugenol

Other Information

- protect this product from excessive heat and direct sun

Questions or comments?

Call toll free - 1-866-424-6735 (weekdays)

PRESCRIBEDsolutions is DISTRIBUTED BY BIOPELLE, INC., A FERNDALE PHARMA GROUP COMPANY, FERNDALE, MI 48220.

www.BIOPELLE.com

MADE IN USA

Package Label

Principal Display
Peel Label-Left
Peel Label-Right